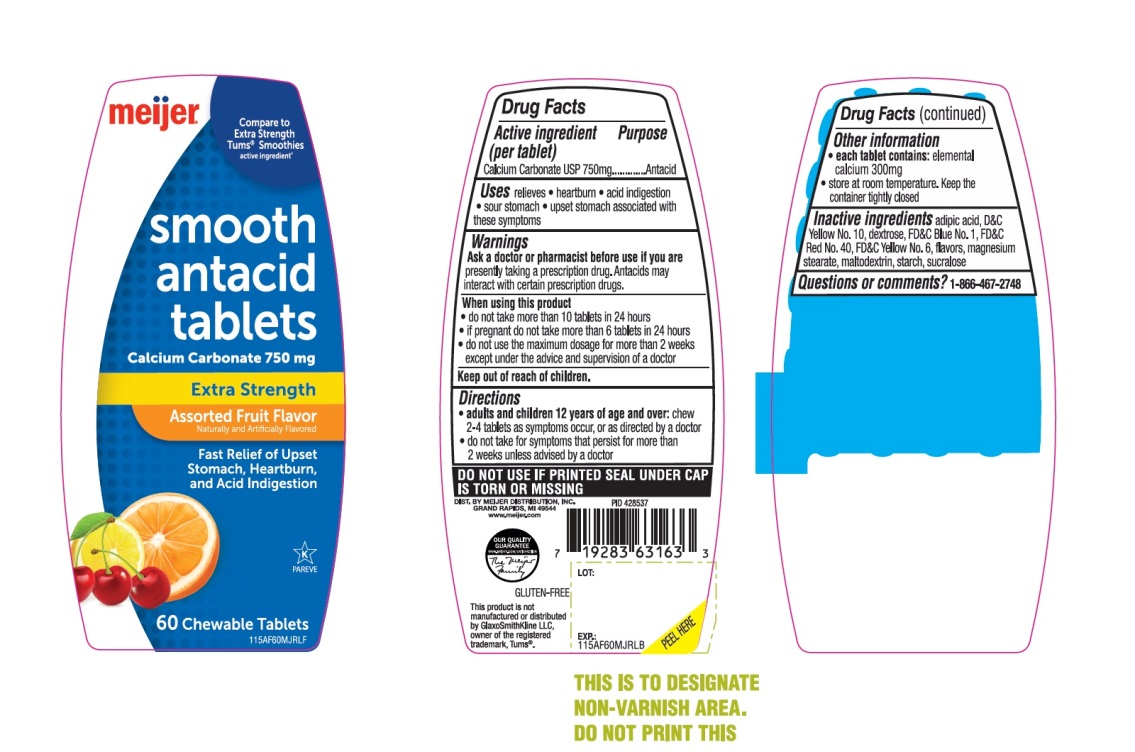 DRUG LABEL: Meijer Extra Strength Smooth Antacid

NDC: 41250-566 | Form: TABLET, CHEWABLE
Manufacturer: MEIJER DISTRIBUTION INC
Category: otc | Type: HUMAN OTC DRUG LABEL
Date: 20251024

ACTIVE INGREDIENTS: CALCIUM CARBONATE 750 mg/1 1
INACTIVE INGREDIENTS: ADIPIC ACID; D&C YELLOW NO. 10; DEXTROSE, UNSPECIFIED FORM; FD&C BLUE NO. 1; FD&C RED NO. 40; FD&C YELLOW NO. 6; MAGNESIUM STEARATE; MALTODEXTRIN; STARCH, CORN; SUCRALOSE

Meijer Extra Strength Smooth Antacid Assorted Fruit Chewable Tablets

ACTIVE INGREDIENT (per tablet)

Calcium Carbonate 750 mg

Purpose

Antacid

Uses

relieves:

- Heartburn
- acid indigestion
- sour stomach
- upset stomach associated with these symptoms

Ask a doctor or pharmacist before use if you are

- presently taking a prescription drug. Antacids may interact with certain prescription drugs.

When using this product

- do not take more than 10 tablets in a 24-hour period
- if pregnant do not take more than 6 tablets in 24 hours
- do not use the maximum dosage for more than 2 weeks except under the advice and supervision of a doctor.

Directions

- adults and children 12 years of age and over:chew 2-4 tablets as symptoms occur, or as directed by a doctor.
- do not take for symptoms that persists for more than 2 weeks unless advised by a doctor

Other information

- each tablet contains:elemental calcium 300 mg
- store at room temperature. keep the container tightly closed.

DO NOT USE IF PRINTED SEAL UNDER CAP IS TORN OR MISSING

Inactive ingredients

adipic acid, D&C Yellow No. 10, dextrose, FD&C Blue No. 1, FD&C Red No. 40, FD&C Yellow No. 6, flavors, magnesium stearate, maltodextrin, starch, sucralose.

Questions or comments?

1-866-467-2748

PRINCIPAL DISPLAY PANEL

meijer®

NDC 41250-566-60

Compare to Extra Strength Tums®Smoothies active ingredient*

Smooth antacid tablets

Calcium Carbonate 750 mg
Extra Strength
Assorted Fruit Flavor

Naturally and Artificially Flavored

Fast Relief of Upset Stomach, Heartburn and Acid Indigestion
60 CHEWABLE TABLETS

GLUTEN-FREE

OUR QUALITY GURANTEE

WWW.MEIJER/SATISFACTION
DIST. BY MEIJER DISTRIBUTION, INC.

GRAND RAPIDS, MI 49544

www.meijer.com

This product is not manufactured or distributed by GlaxoSmithKline LLC, owner of the registered trademark, Tums®.